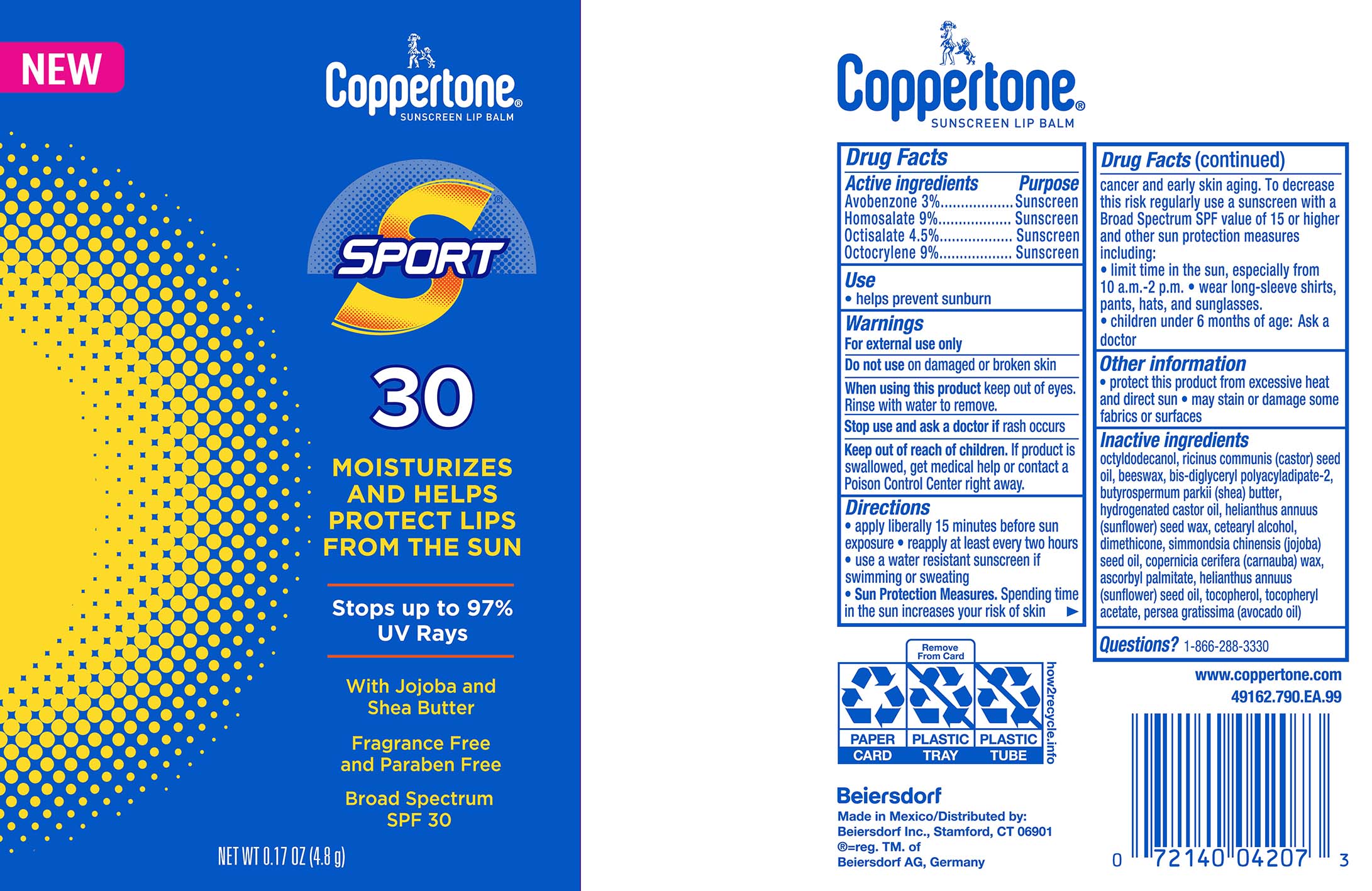 DRUG LABEL: Coppertone Sport Sunscreen Lip Balm SPF 30
NDC: 66800-4207 | Form: STICK
Manufacturer: Beiersdorf Inc
Category: otc | Type: HUMAN OTC DRUG LABEL
Date: 20260106

ACTIVE INGREDIENTS: OCTISALATE 4.5 g/100 g; AVOBENZONE 3 g/100 g; OCTOCRYLENE 9 g/100 g; HOMOSALATE 9 g/100 g
INACTIVE INGREDIENTS: HELIANTHUS ANNUUS SEED WAX; CETOSTEARYL ALCOHOL; HYDROGENATED CASTOR OIL; CARNAUBA WAX; ASCORBYL PALMITATE; SHEA BUTTER; BIS-DIGLYCERYL POLYACYLADIPATE-2; .ALPHA.-TOCOPHEROL ACETATE; TOCOPHEROL; DIMETHICONE; OCTYLDODECANOL; CASTOR OIL; YELLOW WAX; JOJOBA OIL; HELIANTHUS ANNUUS (SUNFLOWER) SEED OIL; AVOCADO OIL

Coppertone Sport Sunscreen Lip Balm SPF 30

Active ingredients:

Avobenzone 3%

Homosalate 9%

Octisalate 4.5%

Octocrylene 9%

Purpose:

Sunscreen

INDICATIONS AND USAGE

Uses • helps prevent sunburn

Warnings:

For external use only

Do not use on damaged or broken skin

When using this product, keep out of eyes. Rinse with water to remove.

Stop use and ask a doctor if rash occurs

Keep out of reach of children. If swallowed, get medical help or contact a
Poison Control Center right away

DOSAGE AND ADMINISTRATION

For sunscreen use

- apply liberally at least 15 minutes before sun exposure
- use a water resistant sunscreen if swimming or sweating
- reapply at least every two hours
- Sun Protection Measures. Spending time in the sun increases your risk of skin cancer and early skin aging. To decrease this risk regularly use a sunscreen with a Broad Spectrum SPFvalue of 15 or higher and other sun protection measures including: •limit time in the sun, especially from 10 a.m. – 2 p.m. •wear long-sleeved shirts, pants, hats, and sunglasses
- children under 6 months of age: Ask a doctor

Inactive ingredients
Octyldodecanol, Ricinus Communis (Castor) Seed Oil, Beeswax, Bis-Diglyceryl Polyacyladipate-2, Butyrospermum Parkii (Shea) Butter, Hydrogenated Castor OIl, Helianthus Annuus (Sunflower) Seed Wax, Cetearyl Alcohol, Dimethicone, Simmondsia Chinensis (Jojoba) Seed Oil, Copernicia Cerifera (Carnauba) Wax, Ascorbyl Palmitate, Helianthus Annuus (Sunflower) Seed Oil, Tocopherol., Tocopheryl Acetate, Persea Gratissima (Avocado) Oil

Questions? 1-866-288-3330

PACKAGE LABEL

Coppertone

Sunscreen Lip Balm

Sport 30

Moisturizes and Helps Protect Lips From The Sun

Stops up to 97%

UV Rays

With Jojoba and Shea Butter

Fragrance Free and Paraben Free

Broad Spectrum SPF 30

NET WT 0.17 OZ (4.8g)